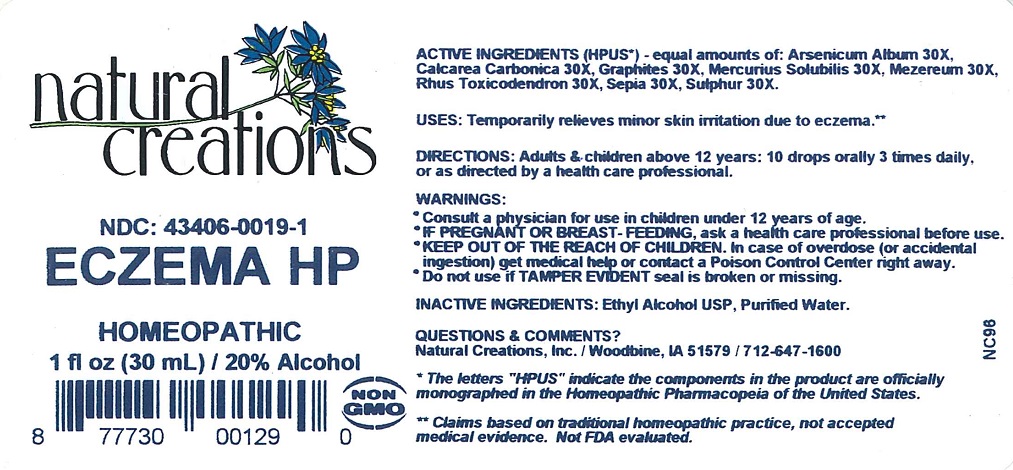 DRUG LABEL: ECZEMA HP
NDC: 43406-0019 | Form: LIQUID
Manufacturer: Natural Creations, Inc.
Category: homeopathic | Type: HUMAN OTC DRUG LABEL
Date: 20230105

ACTIVE INGREDIENTS: ARSENIC TRIOXIDE 30 [hp_X]/1 mL; OYSTER SHELL CALCIUM CARBONATE, CRUDE 30 [hp_X]/1 mL; GRAPHITE 30 [hp_X]/1 mL; MERCURIUS SOLUBILIS 30 [hp_X]/1 mL; DAPHNE MEZEREUM BARK 30 [hp_X]/1 mL; TOXICODENDRON PUBESCENS LEAF 30 [hp_X]/1 mL; SEPIA OFFICINALIS JUICE 30 [hp_X]/1 mL; SULFUR 30 [hp_X]/1 mL
INACTIVE INGREDIENTS: WATER; ALCOHOL

ECZEMA HP

ACTIVE INGREDIENT

ACTIVE INGREDIENTS (HPUS*) - equal amounts of: Arsenicum Album 30X, Calcarea Carbonica 30X, Graphites 30X, Mercurius Solubilis 30X, Mezereum 30X, Rhus Toxicodendron 30X, Sepia 30X, Sulphur 30X

INDICATIONS AND USAGE

USES: Temporarily relieves minor skin irritation due to eczema.**

WARNING:

- Consult a physician for use in children under 12 years of age.
- IF PREGNANT OR BREAST-FEEDING, ask a health care professional before use.
- KEEP OUT OF THE REACH OF CHILDREN. In case of overdose (or accidental ingestion) get medical help or contact a Poison Control Center right away.
- Do not use if TAMPER EVIDENT seal is broken or missing.

DOSAGE AND ADMINISTRATION

DIRECTIONS: Adults and children above 12 years: 10 drops orally 3 times daily, or as directed by a health care professional.

REFERENCES

*The letters "HPUS" indicate the components in the product are officially monographed in the Homeopathic Pharmacopeia of the United States.

**Claims based on traditional homeopathic practice, not accepted medical evidence. Not FDA evaluated.

INACTIVE INGREDIENTS: Purified Water, USP Ethanol Alcohol 20%

QUESTIONS AND COMMENTS?

Natural Creations / Woodbine, IA 51579 / 712-647-1600

PURPOSE

USES: Temporarily relieves minor skin irritation due to eczema.**

KEEP OUT OF REACH OF CHILDREN

KEEP OUT OF THE REACH OF CHILDREN. In case of overdose (or accidental ingestion) get medical help or contact a Poison Control Center.

PACKAGE LABEL

NDC: 43406-0019-1

ECZEMA HP

HOMEOPATHIC

1 fl oz (3o mL) / 20% Alcohol